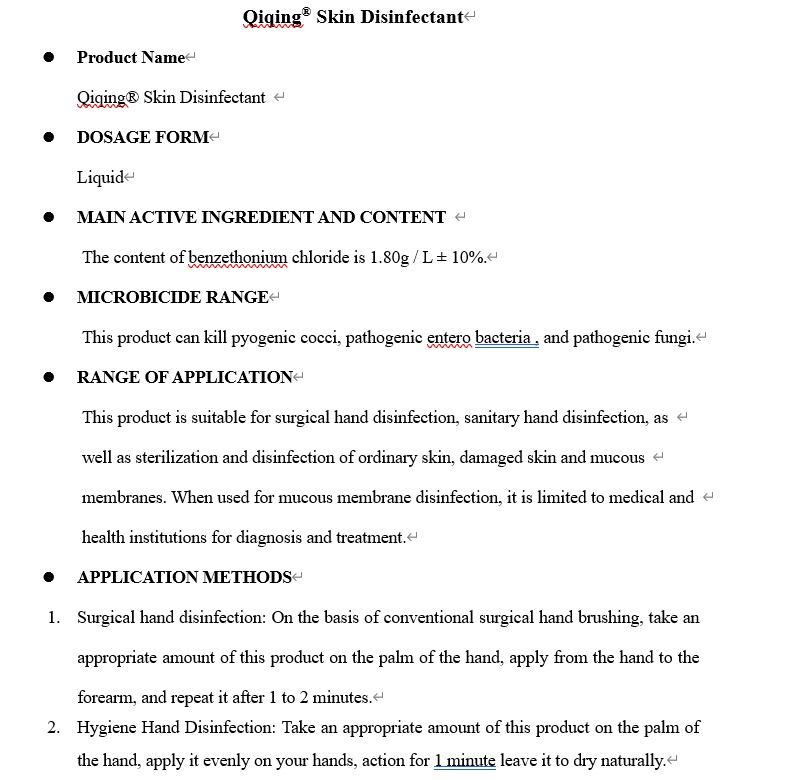 DRUG LABEL: (Qiqing) Skin Disinfectant
NDC: 77919-002 | Form: LIQUID
Manufacturer: QINGDAO PRECISION MEDICAL TECHNOLOGY CO.,LTD. ZIBO BRANCH
Category: otc | Type: HUMAN OTC DRUG LABEL
Date: 20200621

ACTIVE INGREDIENTS: BENZETHONIUM CHLORIDE 1.8 g/1000 mL
INACTIVE INGREDIENTS: WATER; ALLANTOIN 2 g/1000 mL

Qiqing®Skin Disinfectant

ACTIVE INGREDIENT

Benzethonium Chloride 1.80g / L ± 10%

PURPOSE

Antibacterial

WARNINGS

1. This product is an external disinfectant.Prohibition of oral administration. Keep it out of reach of children.

2. Avoid contact with organics and antagonists. Do not use with soap or other anionic detergents, nor use with iodine or peroxides (such as potassium permanganate, hydrogen peroxide, sulfa powder, etc.).

WHEN USING

Avoid contact with organics and antagonists. Do not use with soap or other anionic detergents, nor use with iodine or peroxides (such as potassium permanganate, hydrogen peroxide, sulfa powder, etc.).

Keep out of reach of children. If swallowed, get medical help or contact a Poison Control Center right away

INACTIVE INGREDIENT

Allantoin, Water

DOSAGE AND ADMINISTRATION

Topical Liquid

INDICATIONS AND USAGE

For handwashing to decrease bacteria on the skin